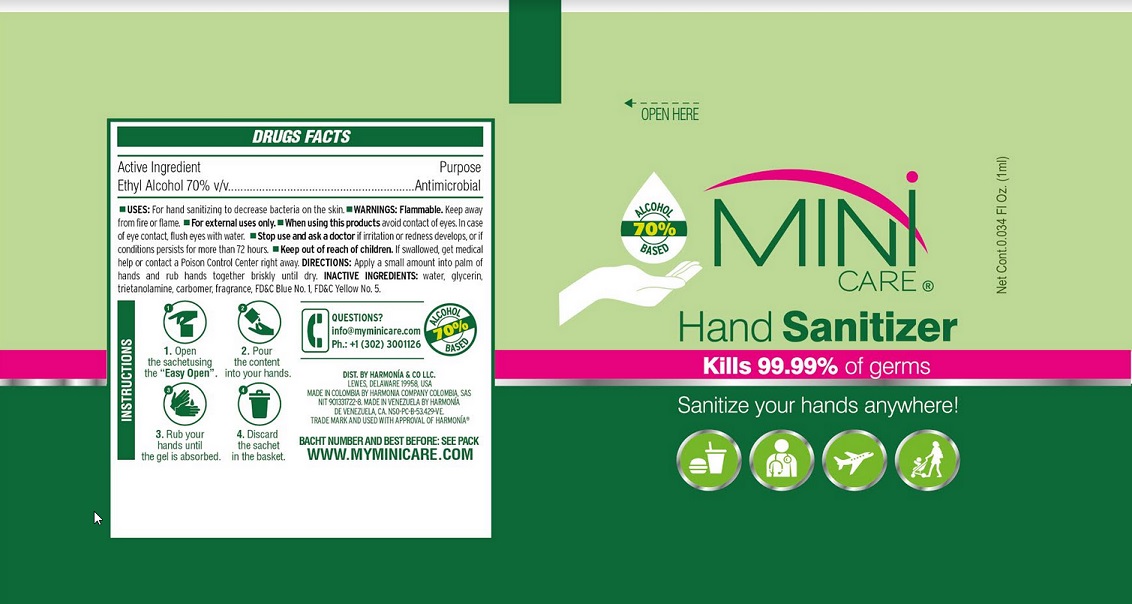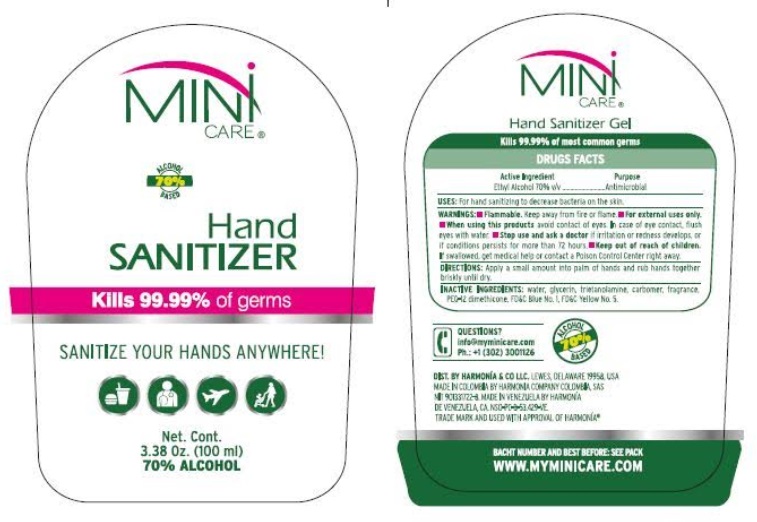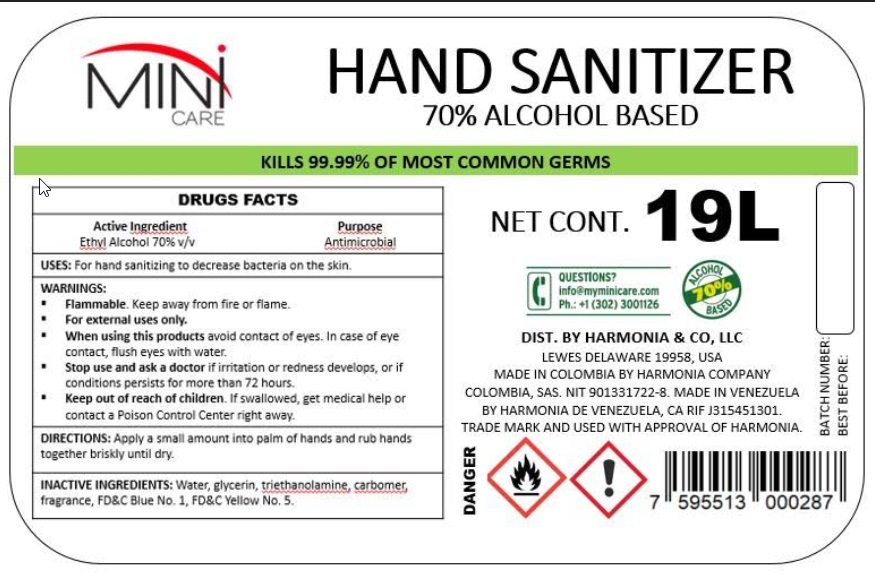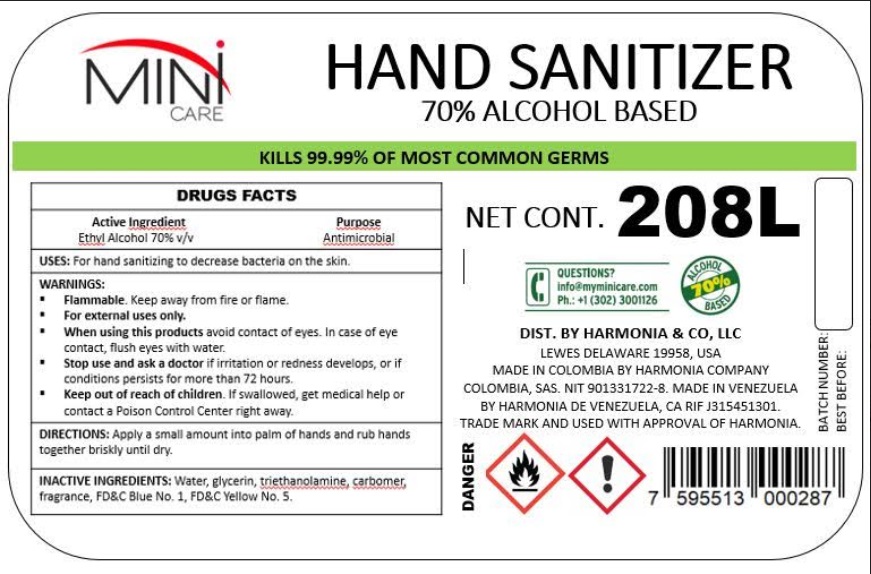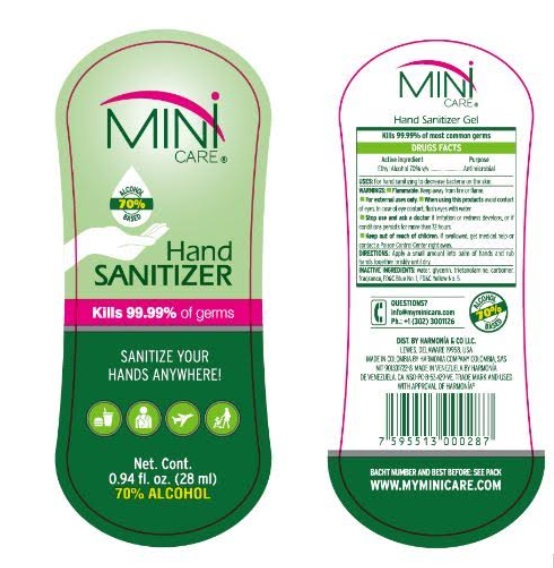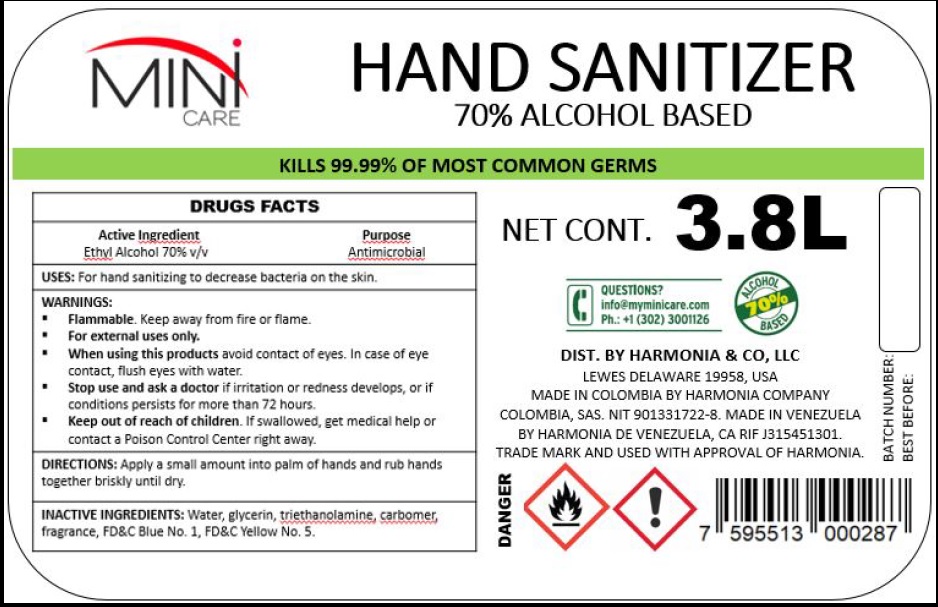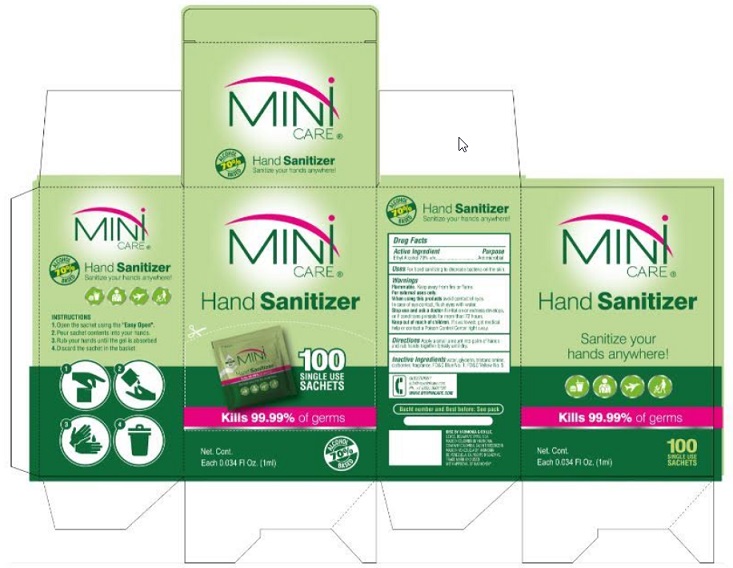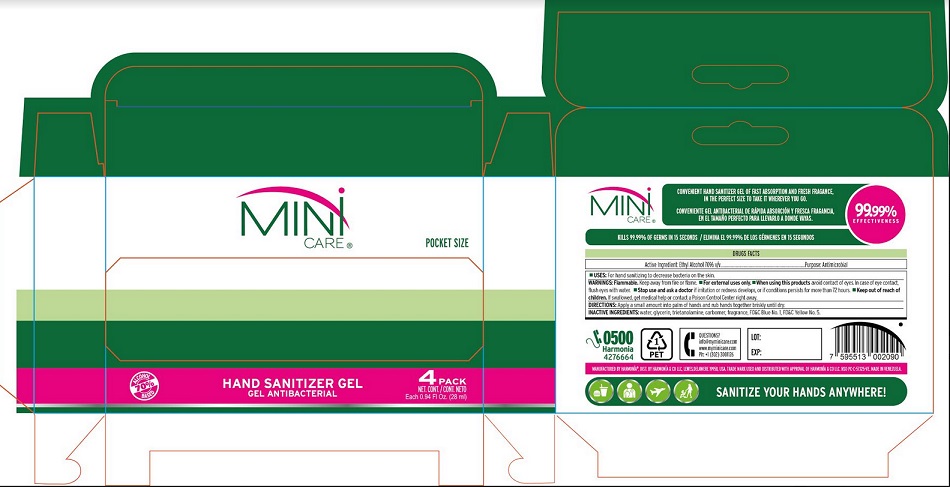 DRUG LABEL: MINI CARE Hand Sanitizer Alcohol
NDC: 73360-004 | Form: GEL
Manufacturer: Harmonia de Venezuela CA
Category: otc | Type: HUMAN OTC DRUG LABEL
Date: 20221230

ACTIVE INGREDIENTS: ALCOHOL 70 mL/100 mL
INACTIVE INGREDIENTS: WATER; GLYCERIN; TROLAMINE; CARBOMER HOMOPOLYMER TYPE C (ALLYL PENTAERYTHRITOL CROSSLINKED); FD&C YELLOW NO. 5; FD&C BLUE NO. 1

Active Ingredient

Ethyl Alcohol 70%

Purpose

Antimicrobial

Use

For hand sanitizing to decrease bacteria on the skin.

Warnings

Flammable. Keep away from fire or flame.

For external uses only.

When using this products avoid contact of eyes. In case of eye contact, flush eyes with water.

Stop use and ask a doctor if irritation or redness develops, or if conditions persists for more than 72 hours.

Keep out of reach of children. If swallowed, get medical help or contact a Poison Control Center right away.

Direction

Apply a small amount into palm of hands and rub hands together briskly until dry.

Inactive ingredients

Water, glycerin, triethanolamine, carbomer, fragrance, FD&amp;C Blue No. 1, FD&amp;C Yellow No. 5

Package Label - Principal Display Panel

1 mL

Pack of 100 (1 mL)

28 mL

Pack of 4 (28 mL)

100 mL

19 Litre

208 Litre